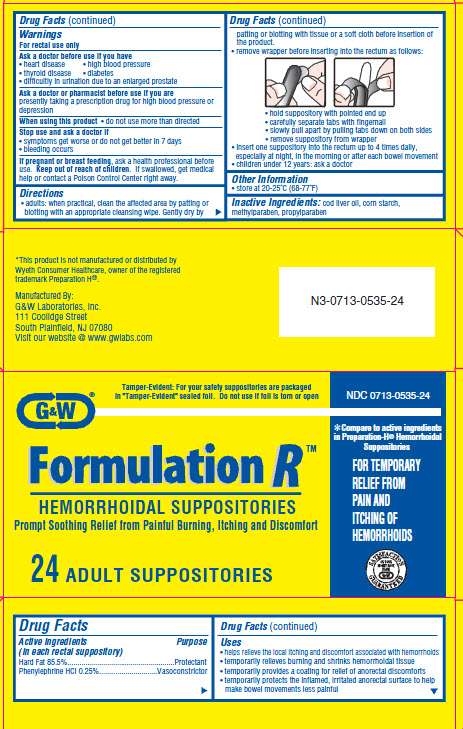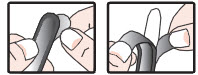 DRUG LABEL: Formulation R 
NDC: 0713-0535 | Form: SUPPOSITORY
Manufacturer: G&W Laboratories, Inc.
Category: otc | Type: HUMAN OTC DRUG LABEL
Date: 20120130

ACTIVE INGREDIENTS: Phenylephrine Hydrochloride 2.5 mg/1 1; Hydrogenated Palm Kernel Oil 855 mg/1 1
INACTIVE INGREDIENTS: Cod Liver Oil; Starch, Corn; Methylparaben; Propylparaben

Formulation RTM Hemorrhoidal Suppositories

ACTIVE INGREDIENT

Hard Fat 85.5%
Phenylephrine HCl 0.25%

PURPOSE

● Protectant
● Vasoconstrictor

USES

• helps relieve the local itching and discomfort associated with hemorrhoids
• temporarily relieves burning and shrinks hemorrhoidal tissue
• temporarily provides a coating for relief of anorectal discomforts
• temporarily protects the inflamed, irritated anorectal surface to help make bowel movements less painful

WARNINGS

For rectal use only
Ask a doctor before use if you have
• heart disease
• high blood pressure
• thyroid disease
• diabetes
• difficulty in urination due to an enlarged prostate
Ask a doctor or pharmacist before use if you are
presently taking a prescription drug for high blood pressure or depression
When using this product
• do not use more than directed
Stop use and ask a doctor if
• symptoms get worse or do not get better in 7 days
• bleeding occurs

IF PREGNANT OR BREAST FEEDING

ask a health professional before use.

KEEP OUT OF REACH OF CHILDREN

If swallowed, get medical help or contact a Poison Control Center right away.

DIRECTIONS

adults: when practical, clean the affected area by patting or blotting with an appropriate cleansing wipe. Gently dry by patting or blotting with tissue or a soft cloth before insertion of the product.
• remove wrapper before inserting into the rectum as follows:
• hold suppository with pointed end up
• carefully separate tabs with fingernail
• slowly pull apart by pulling tabs down on both sides
• remove suppository from wrapper
• insert one suppository into the rectum up to 4 times daily, especially at night, in the morning or after each bowel movement
• children under 12 years: ask a doctor

OTHER INFORMATION

• store at 20-25˚C (68-77˚F)

INACTIVE INGREDIENT

cod liver oil, corn starch, methylparaben, propylparaben

PACKAGE LABEL.PRINCIPAL DISPLAY PANEL

NDC 0713-0535-24
G&W Formulation RTM HEMORRHOIDAL SUPPOSITORIES
Prompt Soothing Relief from Painful Burning, Itching and Discomfort
24 ADULT SUPPOSITORIES
Tamper-Evident: For your safety suppositories are packaged in "Tamper-Evident" sealed foil. Do not use if foil is torn or open
Compare to active ingredients in Preparation-H® Hemorrhoidal Suppositories
FOR TEMPORARY RELIEF FROM PAIN AND ITCHING OF HEMORRHOIDS